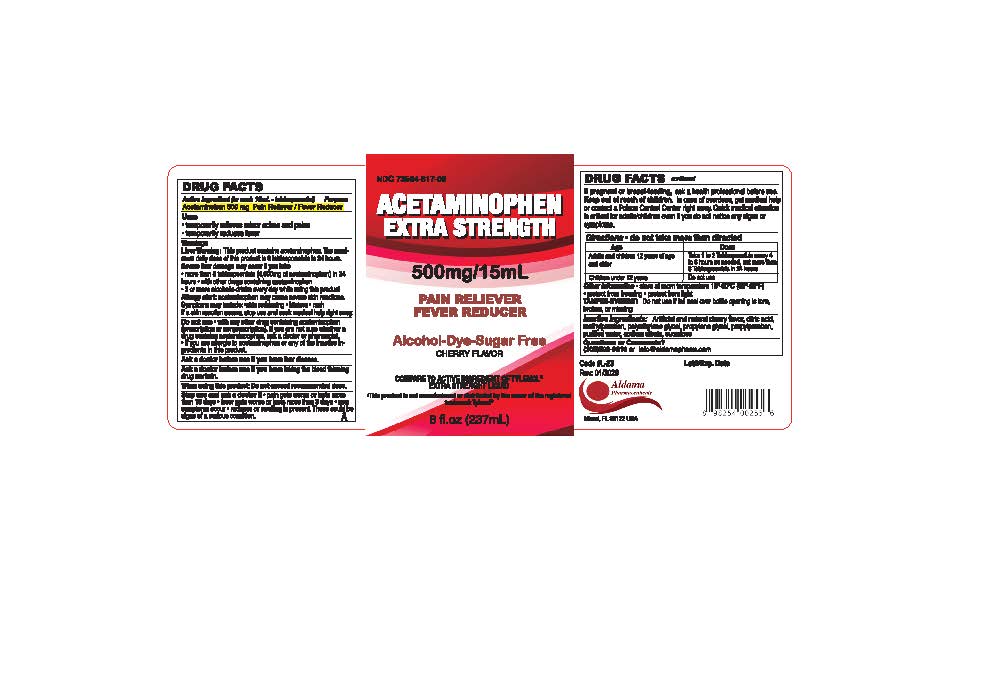 DRUG LABEL: Acetaminophen Extra Strength
NDC: 73564-817 | Form: SOLUTION
Manufacturer: Aldama Pharmaceuticals, Inc
Category: otc | Type: HUMAN OTC DRUG LABEL
Date: 20260120

ACTIVE INGREDIENTS: ACETAMINOPHEN 500 mg/15 mL
INACTIVE INGREDIENTS: WATER; SUCRALOSE; ANHYDROUS CITRIC ACID; POLYETHYLENE GLYCOL 350; PROPYLENE GLYCOL; METHYLPARABEN; PROPYLPARABEN; SODIUM CITRATE

Acetaminophen Extra Strength

Active ingredient (in each 15 mL-teaspoonful)

Acetaminophen 500 mg

Purpose

Pain reliever/fever reducer

Uses

- Temporarily relieves minor aches and pains
  - temporarily reduces fever

Warnings

Liver warning

This product contains acetaminophen. The maximum daily dose of this product is 6 tablespoonfuls in 24 hours. Severe liver damage may occur if:you take

- more than 8 tablespoonfuls (4,000mg of acetaminophen) in 24 hours
- with other drugs containing acetaminophen
- 3 or more alcoholic drinks everyday while using the product.

Allergy alert:Acetaminophen may cause severe skin reactions. Symptoms may include:

- skin reddening
- blisters
- rash

If a skin reaction occurs, stop use and seek medical help right away.

Do not use

- with any other drug containing acetaminophen (prescription or nonprescription). If you are not sure whether a drug contains acetaminophen, ask a doctor or pharmacist.
- if you are allergic to acetaminophen or any of the inactive ingredients in this product.

Ask a doctor before use if your childhas liver disease

Ask a doctor before use if you have taking the blood thinning drug warfarin.

When using this product do not exceed recommended dose

Stop use and ask a doctor if

- pain gets worse or lasts more than 10 days
- fever gets worse or lasts more than 3 days
- new symptoms occur
- redness or swelling is present

These could be signs of a serious condition.

Keep out of reach of children.

In case of overdose, get medical help or conbtact a Poison Control Center right away. Quick medical attention is critical for adults/children even if you do not notice any signs or symptoms

If pregnant or breast-feeding

ask a health professional before use

Directions

- do not take more than directed

Age | DOSE
Adults and children 12 years of age and older | Take 1 to 2 tablespoonfuls every 4 to 6 hours as needed, not more than 6 Tablespoonfuls in 24 hours
Children under 12 years | Do not use

Other information

- store at room temperature between 15-30°C (59-86°F)
- protect from freezing
- protect from light
- TAMPER EVIDENT do not use if foil seal over bottle opening is torn, broken or missing

Inactive Ingredient

artificial and natural cherry flavor, citric acid, methylparaben, polyethylene glycol, propylene glycol, propylparaben, purified water, sodium citrate, sucralose

QUESTIONS

Question or Comments?

call 305-592-9216 or info@aldamapharm.com